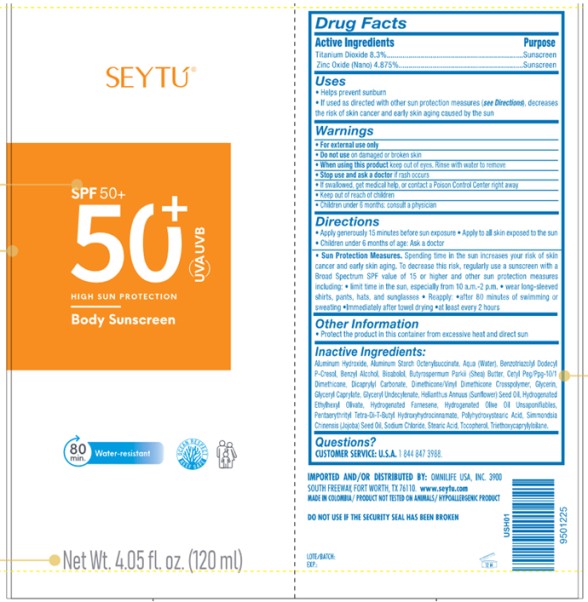 DRUG LABEL: SEYTU Body Sunscreen
NDC: 84271-001 | Form: CREAM
Manufacturer: Omnilife USA, Inc.
Category: otc | Type: HUMAN OTC DRUG LABEL
Date: 20260205

ACTIVE INGREDIENTS: TITANIUM DIOXIDE 8.3 g/100 mL; ZINC OXIDE 4.875 g/100 mL
INACTIVE INGREDIENTS: WATER; DICAPRYLYL CARBONATE; HYDROGENATED OLIVE OIL; GLYCERIN; FARNESENE; SODIUM CHLORIDE; POLYHYDROXYSTEARIC ACID (2300 MW); BENZOTRIAZOLYL DODECYL P-CRESOL; ALUMINUM STARCH OCTENYLSUCCINATE; ALUMINUM HYDROXIDE; CETYL PEG/PPG-10/1 DIMETHICONE (HLB 2); CETYL PEG/PPG-10/1 DIMETHICONE (HLB 3); CETYL PEG/PPG-10/1 DIMETHICONE (HLB 4); CETYL PEG/PPG-10/1 DIMETHICONE (HLB 5); STEARIC ACID; SUNFLOWER OIL; DIMETHICONE/VINYL DIMETHICONE CROSSPOLYMER (HARD PARTICLE); DIMETHICONE/VINYL DIMETHICONE CROSSPOLYMER (SOFT PARTICLE); JOJOBA OIL; BENZYL ALCOHOL; HYDROGENATED OLIVE OIL UNSAPONIFIABLES; GLYCERYL CAPRYLATE; SHEA BUTTER; LEVOMENOL; GLYCERYL 1-UNDECYLENATE; GLYCERYL 2-UNDECYLENATE; TRIETHOXYCAPRYLYLSILANE; TOCOPHEROL; PENTAERYTHRITOL TETRAKIS(3-(3,5-DI-TERT-BUTYL-4-HYDROXYPHENYL)PROPIONATE)

SEYTU BODY SUNSCREEN SPF 50

SEYTÚ BODY SUNSCREEN SPF 50+- titanium dioxide, zinc oxide cream

Drug Facts

Active Ingredients

Titanium Dioxide | 8.3%
Zinc Oxide | 4.875%

Purpose

Sunscreen

Uses

- Helps prevent sunburn.
- If used as directed with other sun protection measures (see Directions), decreases the risk of skin cancer and early skin aging caused by the sun.

Stop use and ask a doctor

if rash occurs.

Warnings

- For external use only.
- Do not use on damaged or broken skin.
- When using this product keep out of eyes. Rinse with water to remove.
- If swallowed, get medical help, or contact a Poison Control Center right away.

Directions

- Apply generously 15 minutes before sun exposure.
- Apply to all skin exposed to the sun.
- Children under 6 months of age: Ask a doctor.
- Sun Protection Measures. Spending time in the sun increases your risk of skin cancer and early skin aging. To decrease this risk, regularly use a sunscreen with a Broad Spectrum SPF value of 15 or higher and other sub and other sun protection measures including:
- Limit time in the sun, especially from 10 a.m.- 2 p.m.
- Wear long-sleeved shirts, pants, hats and sunglasses.
- Reapply: ⦁ after 80 minutes of swimming or sweating. ⦁ Immediately after towel drying ⦁ at least every 2 hours.

Other information

- Protect the product in this container from excessive heat and direct sun.

Inactive Ingredients

Aluminum Hydroxide, Aluminum Starch Octenylsuccinate, Aqua (Water), Benzotriazolyl Dodecyl p-Cresol, Benzyl alcohol, Bisabolol, Butyrospermum Parkii (Shea) Butter, Cetyl PEG/PPG-10/1 Dimethicone, Dicaprylyl Carbonate, Dimethicone/Vinyl Dimethicone Crosspolymer, Glycerin, Glyceryl Caprylate, Glyceryl Undecylenate, Helianthus Annuus (Sunflower) Seed Oil, Hydrogenated Ethylhexyl Olivate, Hydrogenated Farnesene, Hydrogenated Olive Oil Unsaponifiables, Pentaerythrityl Tetra-di-t-butyl Hydroxyhydrocinnamate, Polyhydroxystearic Acid, Simmondsia Chinensis (Jojoba) Seed Oil, Sodium Chloride, Stearic Acid, Tocopherol, Triethoxycaprylylsilane.

PRINCIPAL DISPLAY PANEL

SEYTÚ
SPF 50+
50+UVA UVB
HIGH SUN PROTECTION
Body Sunscreen
80 min. Water-resistant
OCEAN RESPECT
REEF SAFE
Net Wt. 4.05 fl. oz. (120 ml)